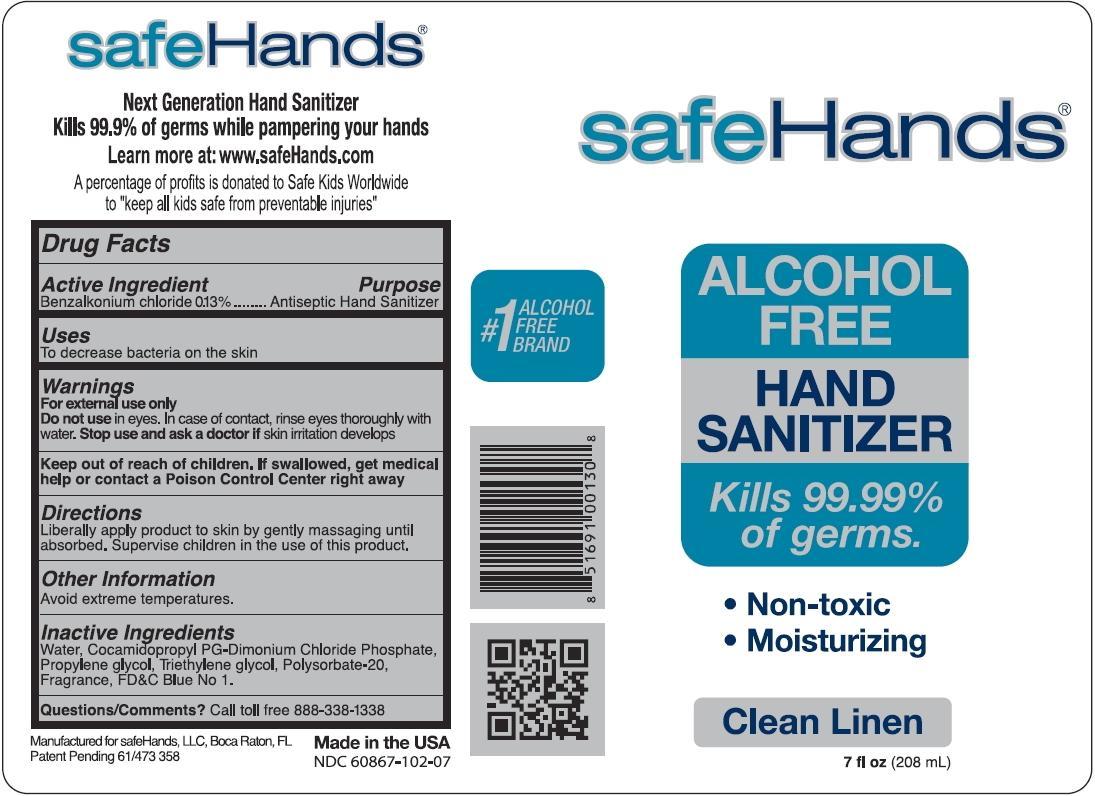 DRUG LABEL: safeHands
NDC: 60867-102 | Form: LIQUID
Manufacturer: safeHands Distribution Ne, LLC
Category: otc | Type: HUMAN OTC DRUG LABEL
Date: 20230608

ACTIVE INGREDIENTS: BENZALKONIUM CHLORIDE 0.13 g/100 mL
INACTIVE INGREDIENTS: Water; COCAMIDOPROPYL PG-DIMONIUM CHLORIDE PHOSPHATE; PROPYLENE GLYCOL; TRIETHYLENE GLYCOL; POLYSORBATE 20; FD&C BLUE NO. 1

Active Ingredient

Benzalkonium chloride, 0.13%

Purpose

Antiseptic hand sanitizer

Uses

To decrease bacteria on the skin.

Warnings

For external use only.

Do not use

in eyes. In case of contact, rinse eyes thoroughly with water.

Stop use and ask a doctor

if skin irritation develops.

Keep out of reach of children

If swallowed, get medical help or contact a Poison Control Center right away.

Directions

Liberally apply product to skin by gently massaging until absorbed. Supervise children in the use of this product.

Other Information

Avoid extreme temperatures.

Inactive Ingredients

Water, Cocamidolpropyl PG-Dimonium Chloride Phospate, Propylene glycol, Triethylene glycol, Polysorbate 20, Fragrance, FD&C Blue No. 1

Questions/Comments?

Call toll free 888-338-1338

safeHands®
Next Generation Hand Sanitizer
Kills 99.9% of germs while pampering your hands
Learn more at: www.safehands.com

A percentage of profits is donated to Safe Kids Worldwide
to “keep all kids safe from preventable injuries”

#1 Alcohol Free Brand

Manufactured for safeHands, LLC, Boca Raton, FL
Patent Pending 61/473 385
Made in the USA

PACKAGE LABEL

safeHands®
Alcohol Free
Hand Sanitizer
Kills 99.9% of germs.
• Non-toxic
• Moisturizing
Clean Linen